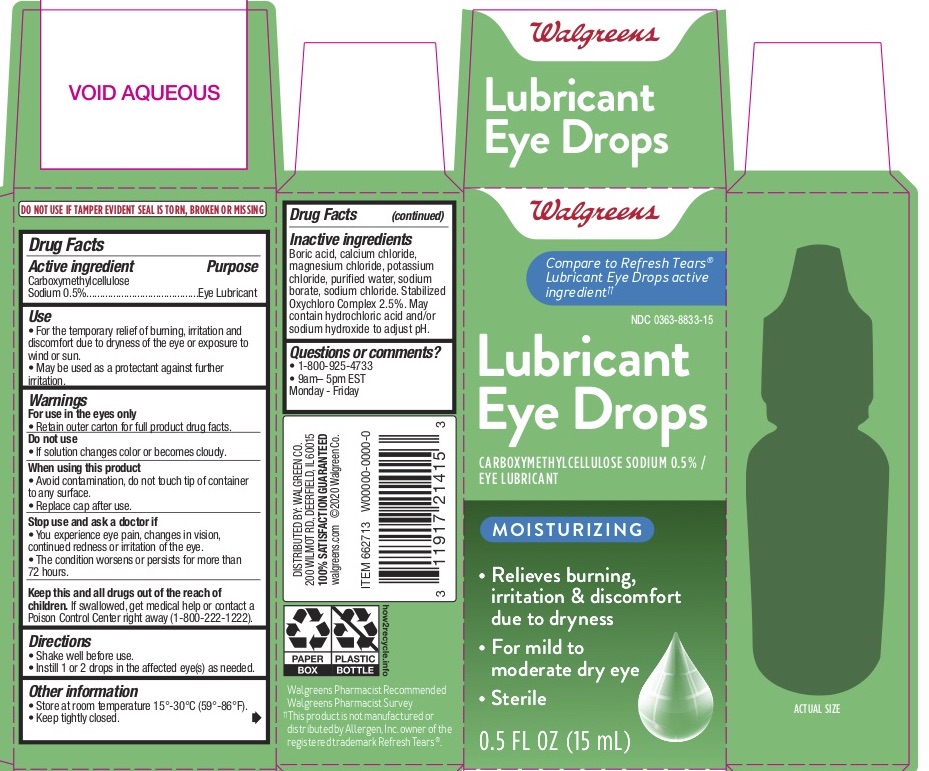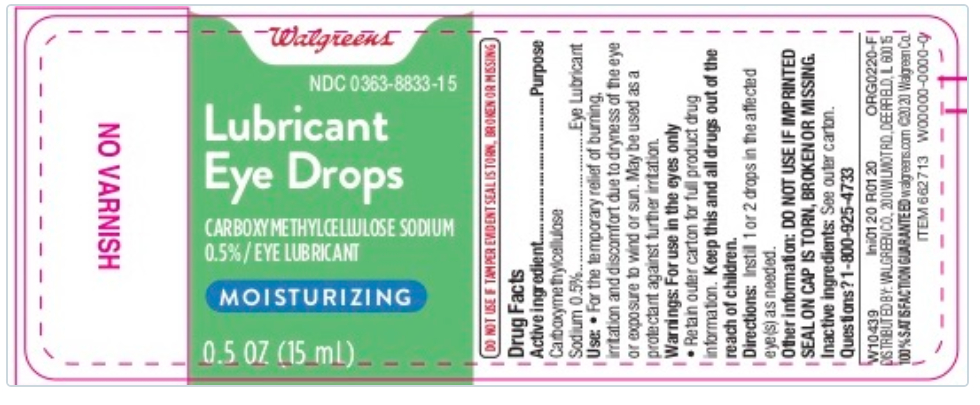 DRUG LABEL: Walgreens Lubricant Eye Drops
NDC: 0363-8833 | Form: SOLUTION/ DROPS
Manufacturer: Walgreen Company
Category: otc | Type: HUMAN OTC DRUG LABEL
Date: 20251119

ACTIVE INGREDIENTS: CARBOXYMETHYLCELLULOSE SODIUM 5 mg/1 mL
INACTIVE INGREDIENTS: BORIC ACID; CALCIUM CHLORIDE; MAGNESIUM CHLORIDE; POTASSIUM CHLORIDE; WATER; SODIUM CHLORITE; SODIUM CHLORATE; CHLORINE DIOXIDE; SODIUM BORATE; SODIUM CHLORIDE; HYDROCHLORIC ACID; SODIUM HYDROXIDE

Walgreens Lubricant Eye Drops
Drug Facts

Active ingredient

Carboxymethylcellulose sodium 0.5%

Purpose

Eye lubricant

Uses

• For the temporary relief of burning, irritation and discomfort due to dryness of the eye or exposure to wind or sun.
• May be used as a protectant against further irritation.

Warnings

For use in the eyes only

• Retain outer carton for full product drug facts.

Stop use and ask a doctor if

• You experience eye pain, changes in vision, continued redness or irritation of the eye.
• The condition worsens or persists for more than 72 hours.

Keep out of reach of children.

If swallowed, get medical help or contact a Poison Control Center right away.

Directions

• Shake well before use.
• Instill 1 or 2 drops in the affected eye(s) as needed.

Other information

- Store at room temperature 15°-30°C (59°-86°F).
- Keep tightly closed.

Inactive ingredients

Boric acid, calcium chloride, magnesium chloride, potassium chloride, purified water, sodium borate, sodium chloride. Stabilized Oxychloro Complex 2.5%. May contain hydrochloric acid and/or sodium hydroxide to adjust pH.

Questions or comments?

• 1-800-925-4733

• 9am– 5pm EST

Monday - Friday

When using this product

• Avoid contamination, do not touch tip of container to any surface.
• Replace cap after use.

PRINCIPAL DISPLAY PANEL

Walgreens Lubricating Eye Drops
0.5 fl oz (15 mL) Sterile